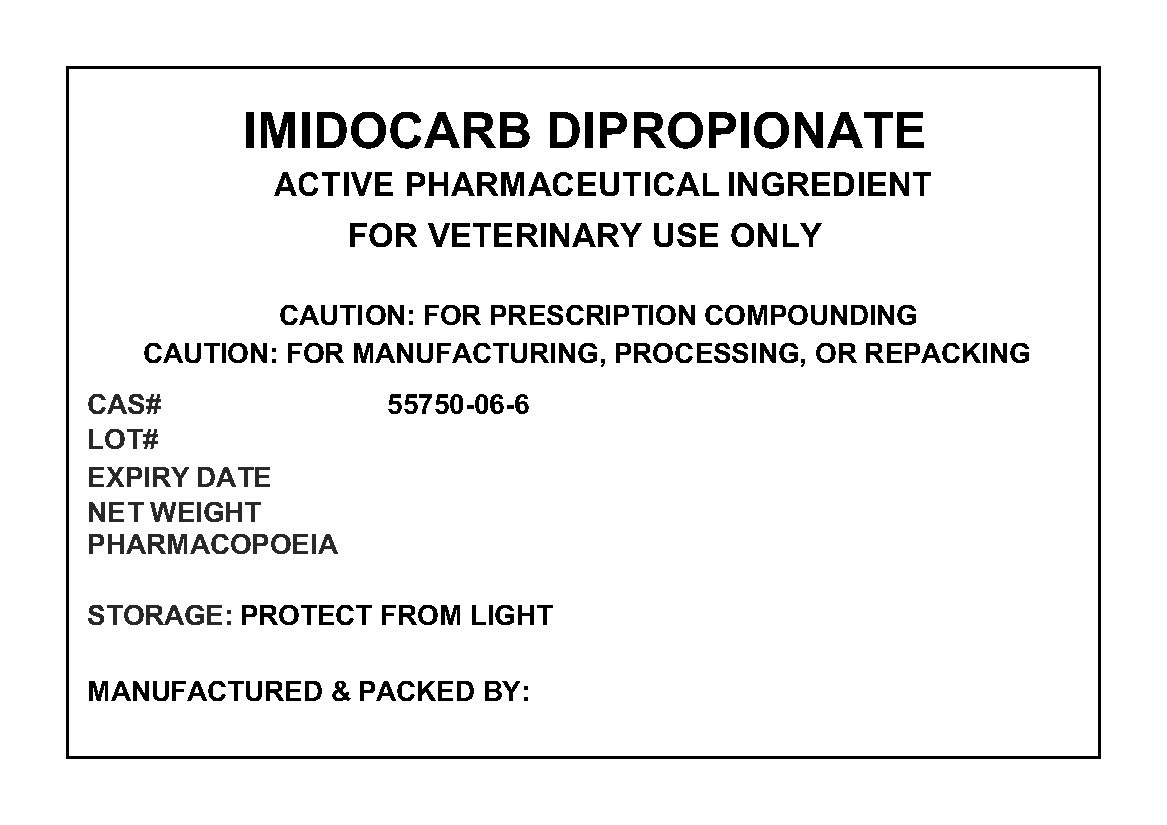 DRUG LABEL: IMIDOCARB DIPROPIONATE
NDC: 72969-096 | Form: POWDER
Manufacturer: PROFESSIONAL GROUP OF PHARMACISTS NEW YORK LLC
Category: other | Type: BULK INGREDIENT
Date: 20201015

ACTIVE INGREDIENTS: IMIDOCARB DIPROPIONATE 1 g/1 g

IMIDOCARB DIPROPIONATE

PACKAGE LABEL

imidocarblabel.jpg